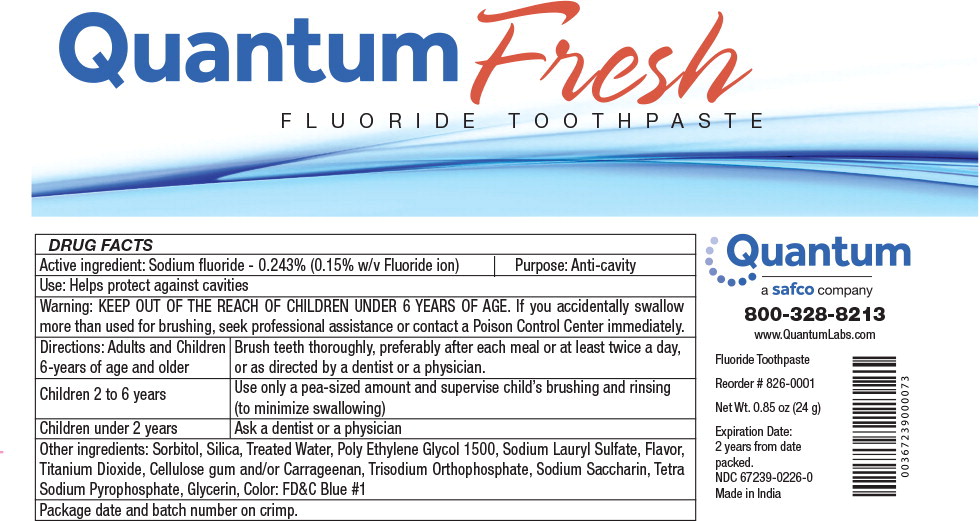 DRUG LABEL: Sodium Fluoride
NDC: 67239-0226 | Form: PASTE, DENTIFRICE
Manufacturer: Safco Dental Supply LLC
Category: otc | Type: HUMAN OTC DRUG LABEL
Date: 20250109

ACTIVE INGREDIENTS: SODIUM FLUORIDE 2.43 mg/1 g
INACTIVE INGREDIENTS: SORBITOL; SILICON DIOXIDE; WATER; GLYCERIN; POLYETHYLENE GLYCOL 1500; SODIUM LAURYL SULFATE; TITANIUM DIOXIDE; CARBOXYMETHYLCELLULOSE SODIUM; CARRAGEENAN; XANTHAN GUM; BUTYL ESTER OF METHYL VINYL ETHER/MALEIC ANHYDRIDE COPOLYMER (125000 MW); SODIUM PHOSPHATE, TRIBASIC, DODECAHYDRATE; SACCHARIN SODIUM; SODIUM PYROPHOSPHATE; SODIUM BENZOATE; METHYLPARABEN; PROPYLPARABEN; BENZYL ALCOHOL; TRICLOSAN; PROPYLENE GLYCOL; SODIUM HYDROXIDE; FD&C BLUE NO. 1

DRUG FACTS

Active ingredient:

Sodium fluoride - 0.243% (0.15% w/v Fluoride ion)

Purpose:

Anti-cavity

Use:

Helps protect against cavities

Warning:

KEEP OUT OF REACH OF CHILDREN

KEEP OUT OF THE REACH OF CHILDREN UNDER 6 YEARS OF AGE. If you accidentally swallow more than used for brushing, seek professional assistance or contact a Poison Control Center immediately.

Directions:

Adults and Children 6-years of age and older

Brush teeth thoroughly, preferably after each meal or at least twice a day, or as directed by a dentist or a physician.

Children 2 to 6 years

Use only a pea-sized amount and supervise child's brushing and rinsing (to minimize swallowing)

Children under 2 years

Ask a dentist or a physician

Other ingredients:

Sorbitol, Silica, Treated Water, Poly Ethylene Glycol 1500, Sodium Lauryl Sulfate, Flavor, Titanium Dioxide, Cellulose gum and/or Carrageenan, Trisodium Orthophosphate, Sodium Saccharin, Tetra Sodium Pyrophosphate, Glycerin, Color: FD&C Blue #1

Package date and batch number on crimp.

Principal Display Panel – 24 g Box Label

Quantum Fresh
FLUORIDE TOOTHPASTE

Quantum

a safco company

800-328-8213

www.QuantumLabs.com

Fluoride Toothpaste

Reorder # 826-0001

Net Wt. 0.85 oz (24 g)

Expiration Date:

2 years from date
packed.

NDC 67239-0226-0

Made in India